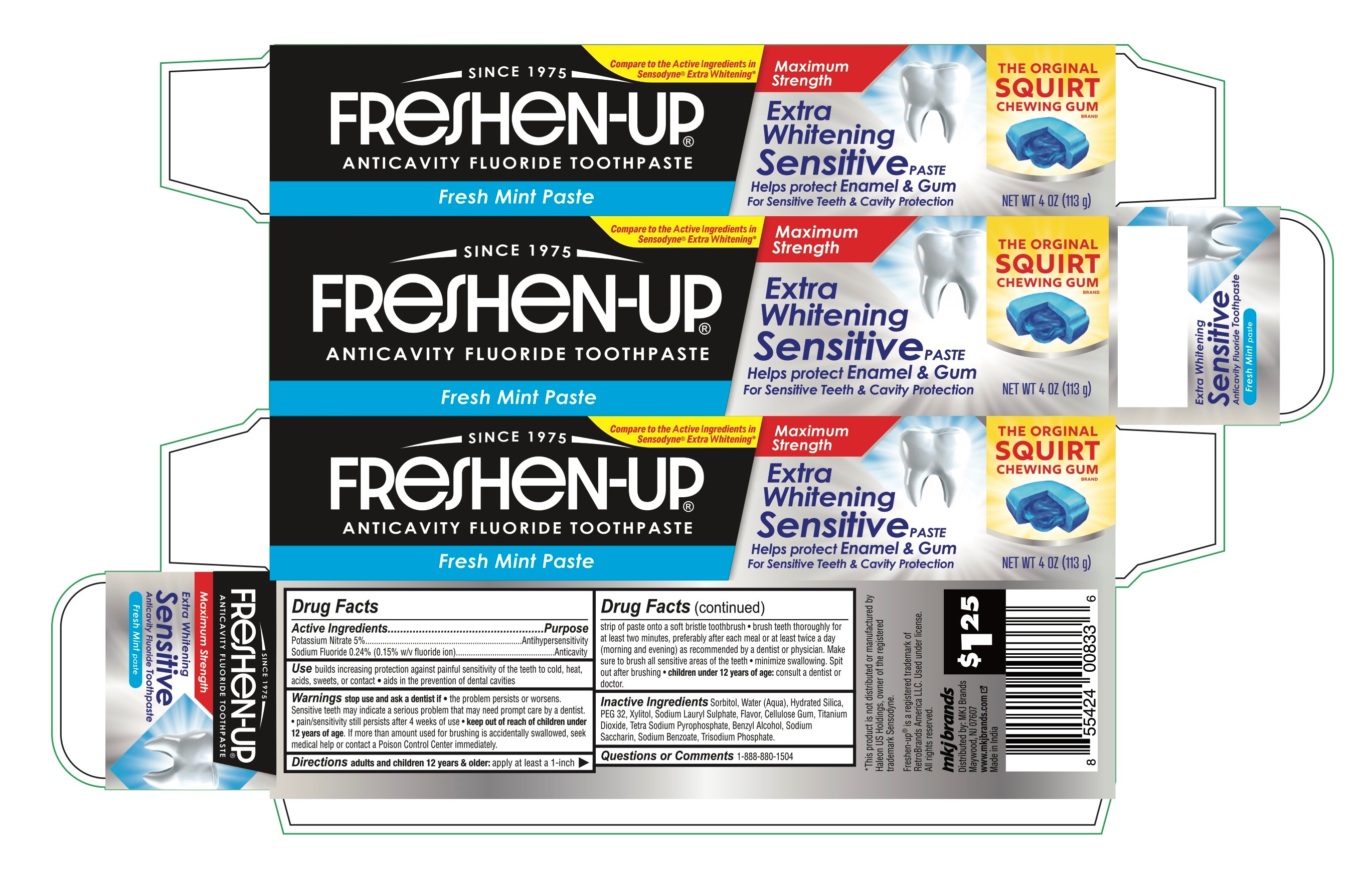 DRUG LABEL: Freshen Up
NDC: 77782-002 | Form: GEL, DENTIFRICE
Manufacturer: MKJ BRANDS LLC
Category: otc | Type: HUMAN OTC DRUG LABEL
Date: 20250612

ACTIVE INGREDIENTS: POTASSIUM NITRATE 5 g/100 g; SODIUM FLUORIDE 24 mg/100 g
INACTIVE INGREDIENTS: BENZYL ALCOHOL; SODIUM LAURYL SULFATE; SODIUM SACCHARIN; SORBITOL; WATER; HYDRATED SILICA; PEG-32; CELLULOSE GUM; TETRASODIUM PYROPHOSPHATE; SODIUM PHOSPHATE, TRIBASIC, ANHYDROUS; XYLITOL; TITANIUM DIOXIDE; SODIUM BENZOATE

Freshen-up Extra Strength Extra Whitening Sensitive Toothpaste

Drug Facts

Active ingredient

Sodium fluoride 0.24% (0.15% w/v fluoride ion)

Potassium Nitrate 5%

Purpose

Anticavity

Antihypersensitivity

Use

builds increasing protection against painful sensitivity of teeth to cold, heat, acids, sweets or contact

aids in prevention of dental cavities

Warnings

Stop use and ask a dentist if the problem persists or worsens, snesitive teeth may indicate a serious problem that may need prompt care by dentist. Pain senstivity still persists after 4 weeks of use

Keep out of reach of children under 6 years of age.If more than used for brushing is accidentally swallowed, get medical help or contact a Poison Control Center right away.

Directions

adults and children 12 years of age and older | apply atleast a 1-inch strip of paste onto a soft bristle toothrush. bursh atleast for 2 minutes preferably after each meal or at least twice a day, or as directed by a dentist or physician. Make sure to brush all sensitve areas of the teeth. minimizi swallowing. Spit out after brushing
children under 12 years and under | ask a dentist or physician

Inactive ingredients

sorbitol, water, hydrated silica, PEG-32, sodium lauryl sulfate, flavor, tetrasodium pyrophosphate, cellulose gum, xlitol, sodium saccharin,titanium dioxide, benzyl alcohol,Tri sodium phosphate, sodium benzoate

Questions?

1-888-880-1504

Dist. by:
MKJ Brands